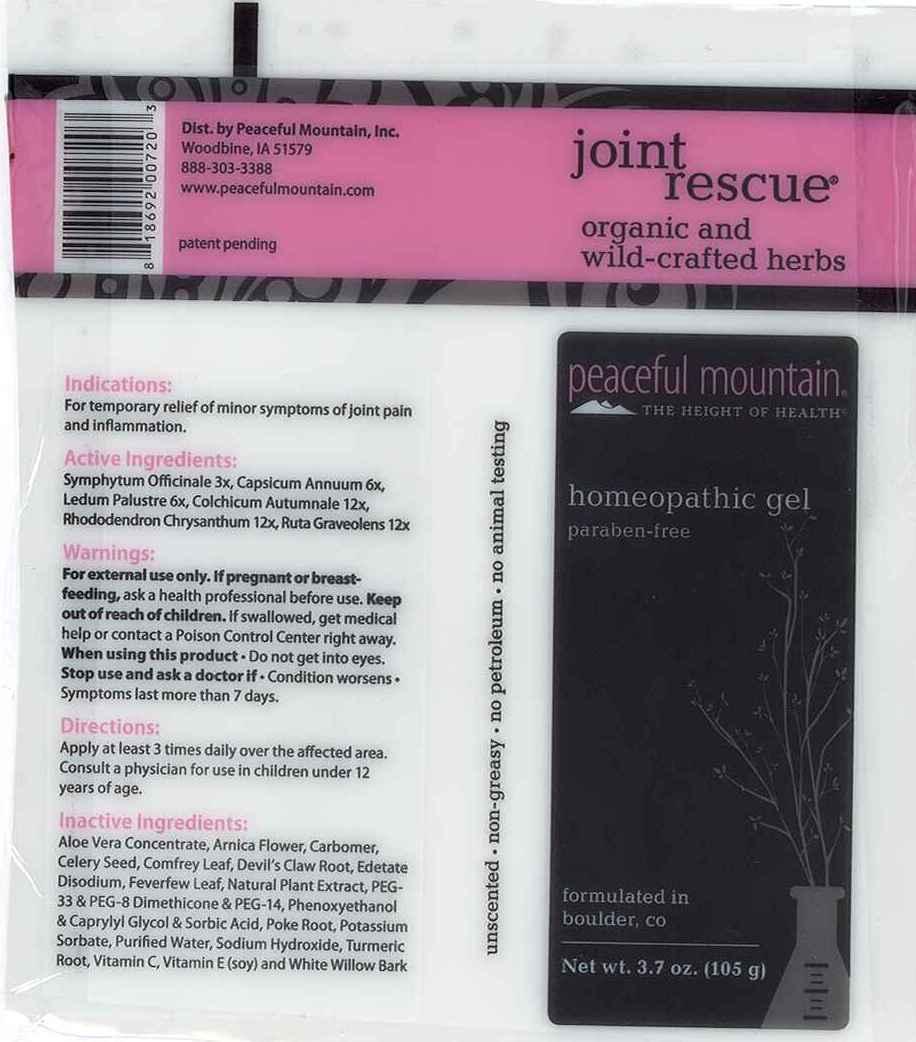 DRUG LABEL: Joint Rescue
NDC: 43846-0013 | Form: GEL
Manufacturer: Peaceful Mountain, Inc.
Category: homeopathic | Type: HUMAN OTC DRUG LABEL
Date: 20240613

ACTIVE INGREDIENTS: COMFREY ROOT 3 [hp_X]/1 g; CAPSICUM 6 [hp_X]/1 g; RHODODENDRON TOMENTOSUM LEAFY TWIG 6 [hp_X]/1 g; COLCHICUM AUTUMNALE BULB 12 [hp_X]/1 g; RHODODENDRON AUREUM LEAF 12 [hp_X]/1 g; RUTA GRAVEOLENS FLOWERING TOP 12 [hp_X]/1 g
INACTIVE INGREDIENTS: ALOE VERA LEAF; ARNICA MONTANA FLOWER; CARBOMER INTERPOLYMER TYPE A (ALLYL SUCROSE CROSSLINKED); CELERY SEED; COMFREY LEAF; HARPAGOPHYTUM PROCUMBENS ROOT; EDETATE SODIUM; FEVERFEW; OREGANO; POLYETHYLENE GLYCOL 1500; PEG-8 DIMETHICONE; POLYETHYLENE GLYCOL 700; PHENOXYETHANOL; CAPRYLYL GLYCOL; SORBIC ACID; PHYTOLACCA AMERICANA ROOT; POTASSIUM SORBATE; WATER; SODIUM HYDROXIDE; TURMERIC; ASCORBIC ACID; .ALPHA.-TOCOPHEROL; SALIX ALBA BARK

Drug Facts

ACTIVE INGREDIENTS

Symphytum Officinale 3X, Capsicum Annuum 6X, Ledum Palustre 6X, Colchicum Autumnale 12X

INDICATIONS

For temporary relief of minor symptoms of joint pain and inflammation.

WARNINGS

For external use only. If pregnant or breast-feeding, ask a health professional before use. Keep out of reach of children. If swallowed, get medical help or contact a Poison Control Center right away. When using this product Do not get into eyes. Stop use and ask a doctor if Condition worsens Symptoms last more than 7 days.

DIRECTIONS

Apply at least 3 times daily over the affected area. Consult a physician for use in children under 12 years of age.

INACTIVE INGREDIENTS

Aloe Vera, Arnica Montana (Flower), Carbomer (Ultrez 21), Celery (seed), Comfrey (leaf), Harpagophytum Procumbens, Edetate Disodium, Feverfew, Origanox WS, PEG 33, PEG 8 Dimethicone, PEG 14, Phenoxyethanol, Caprylyl Glycol, Sorbic Acid, Phytolacca Americana, Potassium Sorbate, Water, Sodium Hydroxide Solution, Turmeric (root), Ascorbic Acid, Vitamin E Oil, Salix Alba (bark)

KEEP OUT OF REACH OF CHILDREN

If swallowed, get medical help or contact a Poison Control Center right away.

INDICATIONS AND USAGE

For temporary relief of minor symptoms of joint pain and inflammation.

QUESTIONS

Dist. by Peaceful Mountain, Inc.

Woodbine, IA 51579

888-303-3388

www.peacefulmountain.com

PACKAGE LABEL

joint rescue

organic and wild crafted herbs

peaceful mountain

THE HEIGHT OF HEALTH

homeopathic gel

paraben-free

formulated in boulder, co

Net wt. 3.7 oz (105 g)